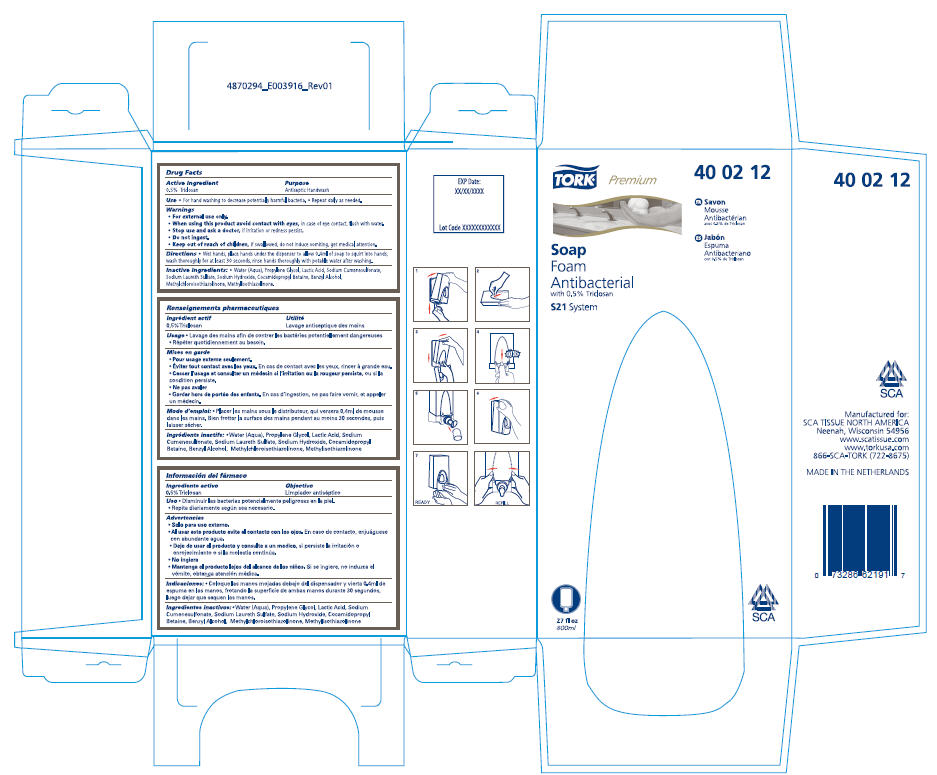 DRUG LABEL: Tork Premium
NDC: 49351-015 | Form: LIQUID
Manufacturer: SCA Tissue North America
Category: otc | Type: HUMAN OTC DRUG LABEL
Date: 20100329

ACTIVE INGREDIENTS: Triclosan 0.5 g/100 mL
INACTIVE INGREDIENTS: Water; Propylene Glycol; Lactic Acid; Sodium Laureth Sulfate; Sodium Hydroxide; Cocamidopropyl Betaine; Benzyl Alcohol; Methylchloroisothiazolinone; Methylisothiazolinone

TORK®
Soap
Foam
Antibacterial

Drug Facts

Active Ingredient

0.5% Triclosan

Purpose

Antiseptic Handwash

Use

- For hand washing to decrease potentially harmful bacteria.
- Repeat daily as needed.

Warnings

- For external use only.
- When using this product avoid contact with eyes, in case of eye contact, flush with water.
- Stop use and ask a doctor, if irritation or redness persist.
- Do not ingest.
- Keep out of reach of children, if swallowed, do not induce vomiting, get medical attention.

Directions

- Wet hands, place hands under the dispenser to allow 0.4ml of soap to squirt into hands, wash thoroughly for at least 30 seconds, rinse hands thoroughly with potable water after washing.

Inactive Ingredients

- Water (Aqua), Propylene Glycol, Lactic Acid, Sodium Cumenesulfonate, Sodium Laureth Sulfate, Sodium Hydroxide, Cocamidopropyl Betaine, Benzyl Alcohol, Methylchloroisothiazolinone, Methylisothiazolinone.

Manufactured for:
SCA TISSUE NORTH AMERICA
Neenah, Wisconsin 54956
www.scatissue.com
www.torkusa.com
866-SCA-TORK (722-8675)

PRINCIPAL DISPLAY PANEL - 800 mL Carton

TORK®
Premium
40 02 12

Soap
Foam
Antibacterial
with 0.5% Triclosan

S21 System

FR Savon
Mousse
Antibactérian
avec 0.5% de Triclosan

ES Jabón
Espuma
Antibacteriano
con 0.5% de Triclosan

27 fl oz
800ml

SCA